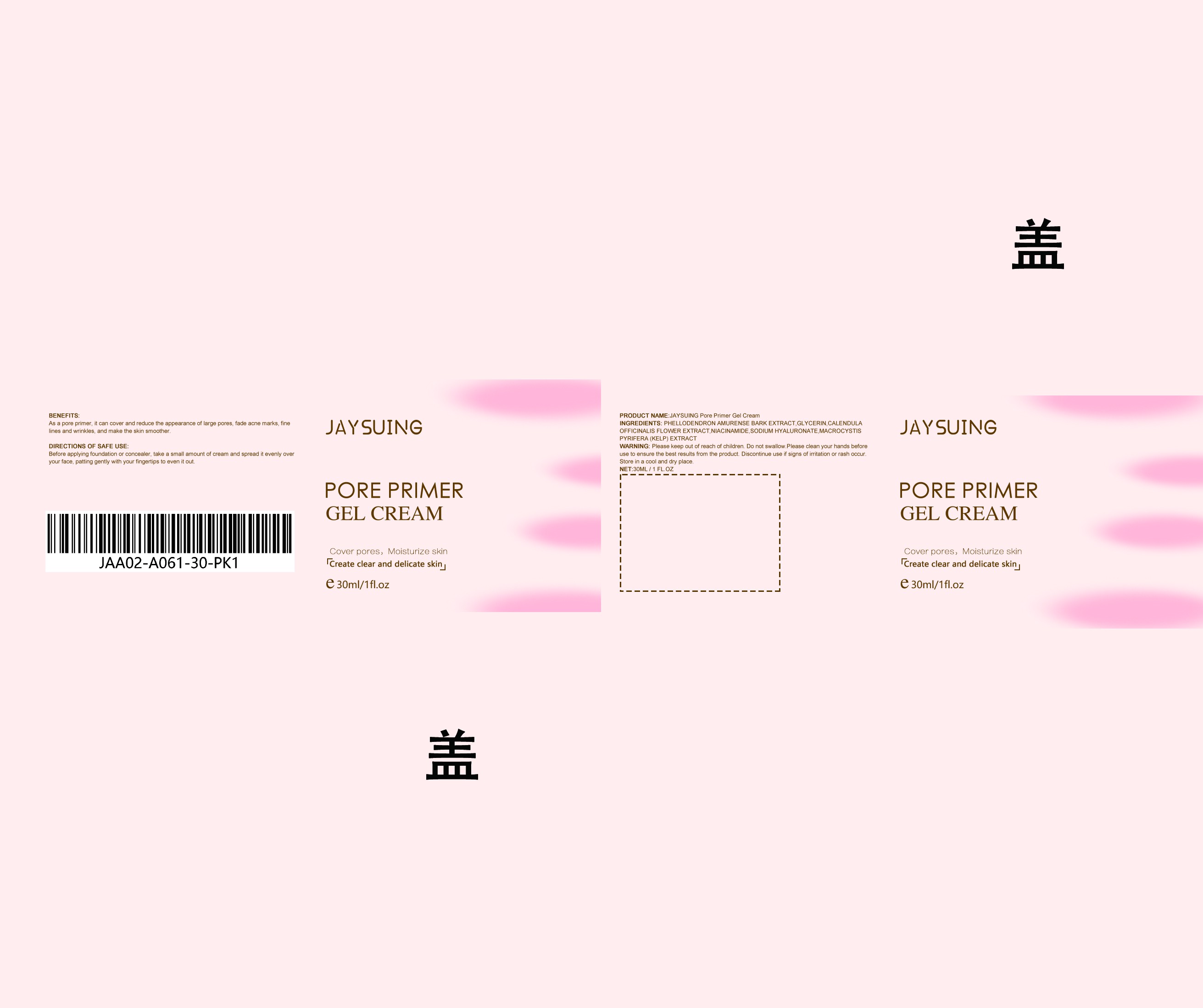 DRUG LABEL: Cream
NDC: 84067-657 | Form: CREAM
Manufacturer: Shantou Youjia E-Commerce Co.,Ltd.
Category: otc | Type: HUMAN OTC DRUG LABEL
Date: 20240504

ACTIVE INGREDIENTS: PHELLODENDRON AMURENSE BARK 9 mg/30 mg
INACTIVE INGREDIENTS: CALENDULA OFFICINALIS FLOWER 4.5 mg/30 mg; NIACINAMIDE 4.5 mg/30 mg; MACROCYSTIS PYRIFERA 3 mg/30 mg; HYALURONATE SODIUM 3 mg/30 mg; GLYCERIN 6 mg/30 mg

JAYSUING Pore Primer Gel Cream